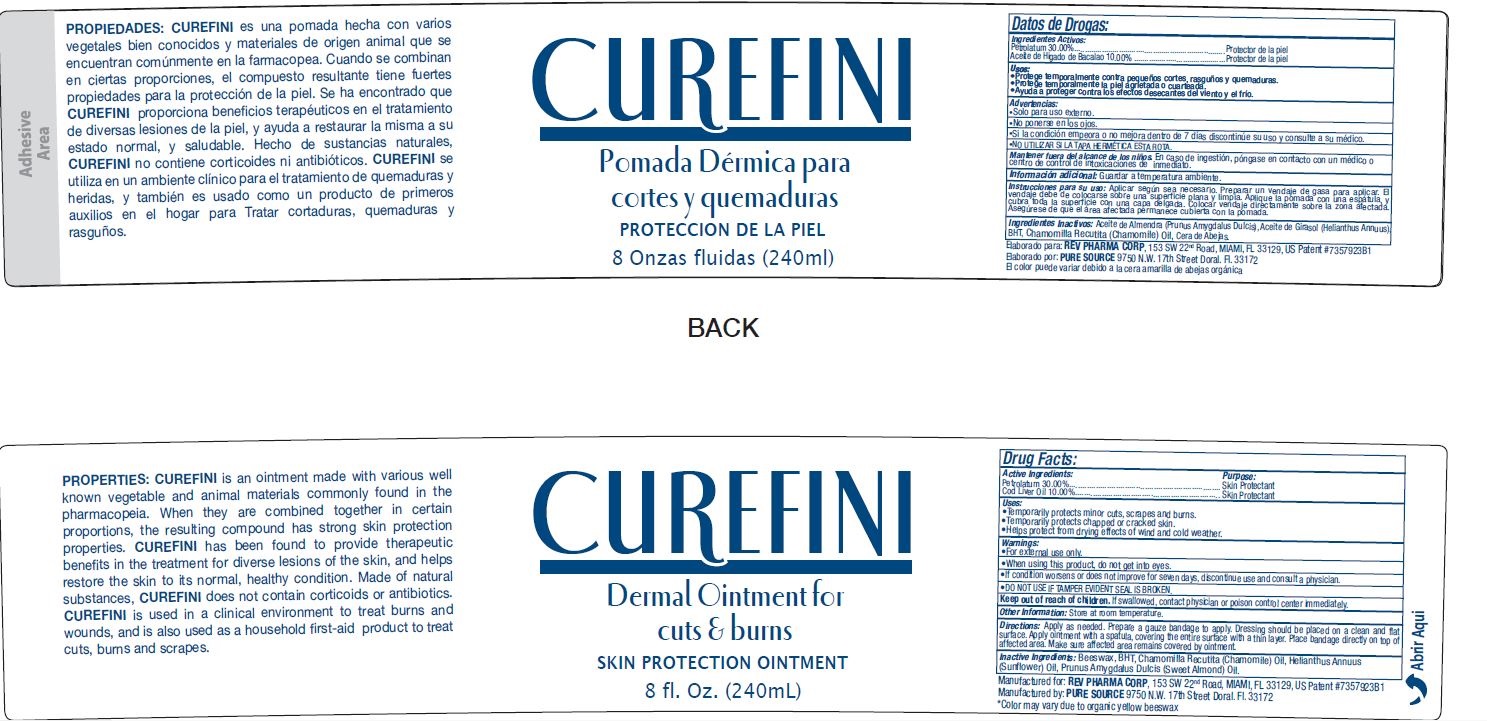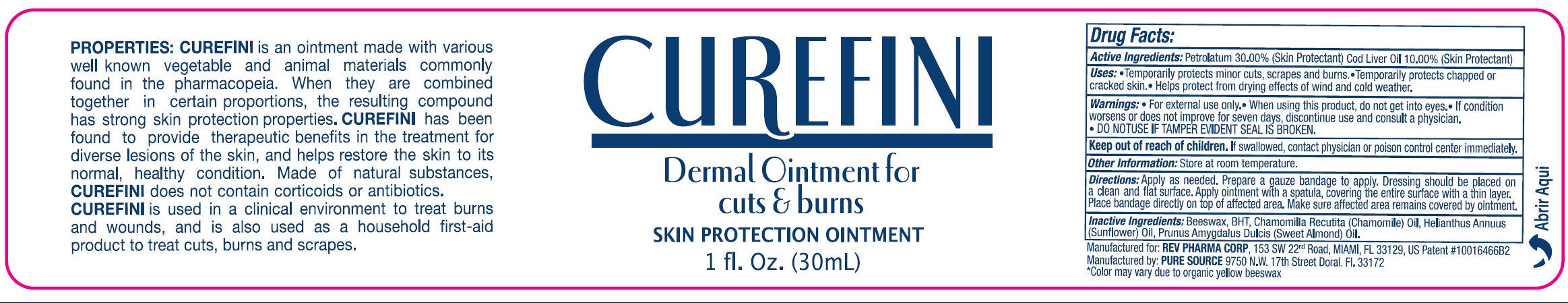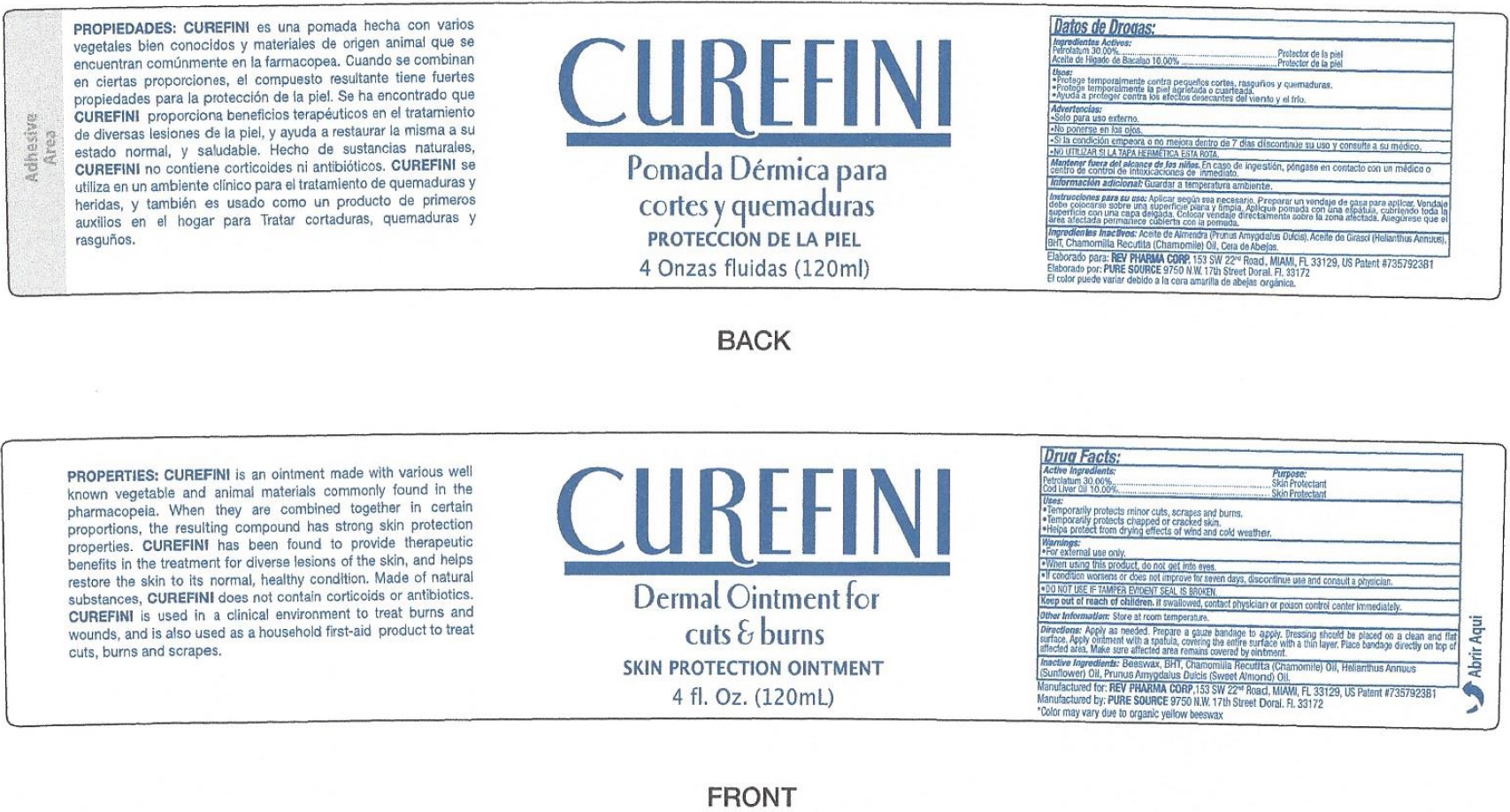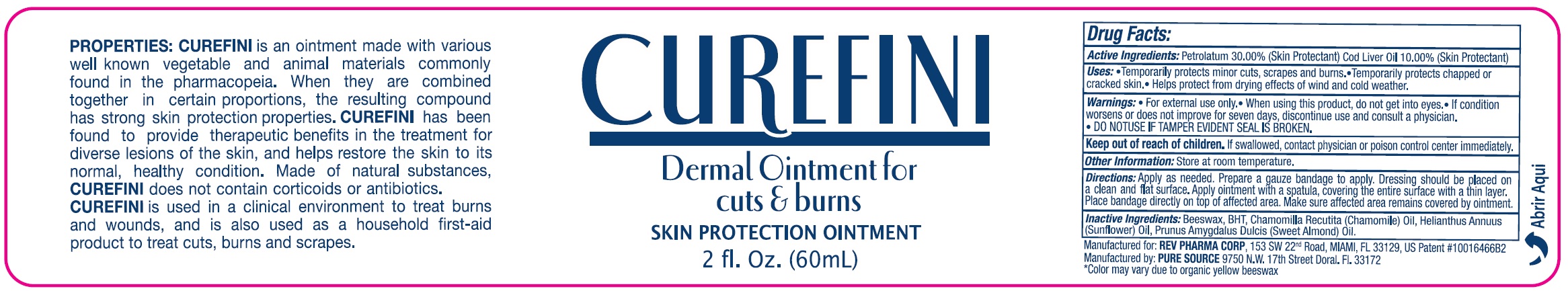 DRUG LABEL: Curefini Dermal
NDC: 69981-754 | Form: OINTMENT
Manufacturer: Rev Pharma Corp
Category: otc | Type: HUMAN OTC DRUG LABEL
Date: 20231105

ACTIVE INGREDIENTS: PETROLATUM 300 mg/1 mL; COD LIVER OIL 100 mg/1 mL
INACTIVE INGREDIENTS: YELLOW WAX; BUTYLATED HYDROXYTOLUENE; CHAMOMILE; HELIANTHUS ANNUUS FLOWERING TOP; ALMOND OIL

Curefini Dermal Ointment

Active Ingredients:

Petrolatum 30.00%, Cod Liver Oil 10.00%

PURPOSE

(Skin Protectant)

Uses:

- Temporarily protects minor cuts, scrapes and burns.
- Temporarily protects chappped or cracked skin.
- Helps protect from drying effects of wind and cold weather.

Warnings:

- For external use only.

When using this product

- do not get into eyes.
- If condition woresens or does not improve for seven days, discontinue use and consult a physician.

DO NOT USE

- IF TAMPER EVIDENT SEAL IS BROKEN.

Keep out of reach of children.

If swallowed, contact physician or poison control center immediately.

Other information:

Store at room temperature.

Directions:

Apply as needed. Prepare a gauze bandaage to apply. Dressing should be placed on a clean and flat surface. Apply ointment with a spatula, covering the entire sufrace with a thin layer. Place bandage directly on top of affected area. Make sure afffected area remains covered by ointment.

Inactive Ingredients:

Beeswax, BHT Chammomilla Recutita (Chammoile)oil, Helianthus Annuus (Sunflower) Oil, Prunus Amgdalus Dulcis (Sweet Almond) Oil.